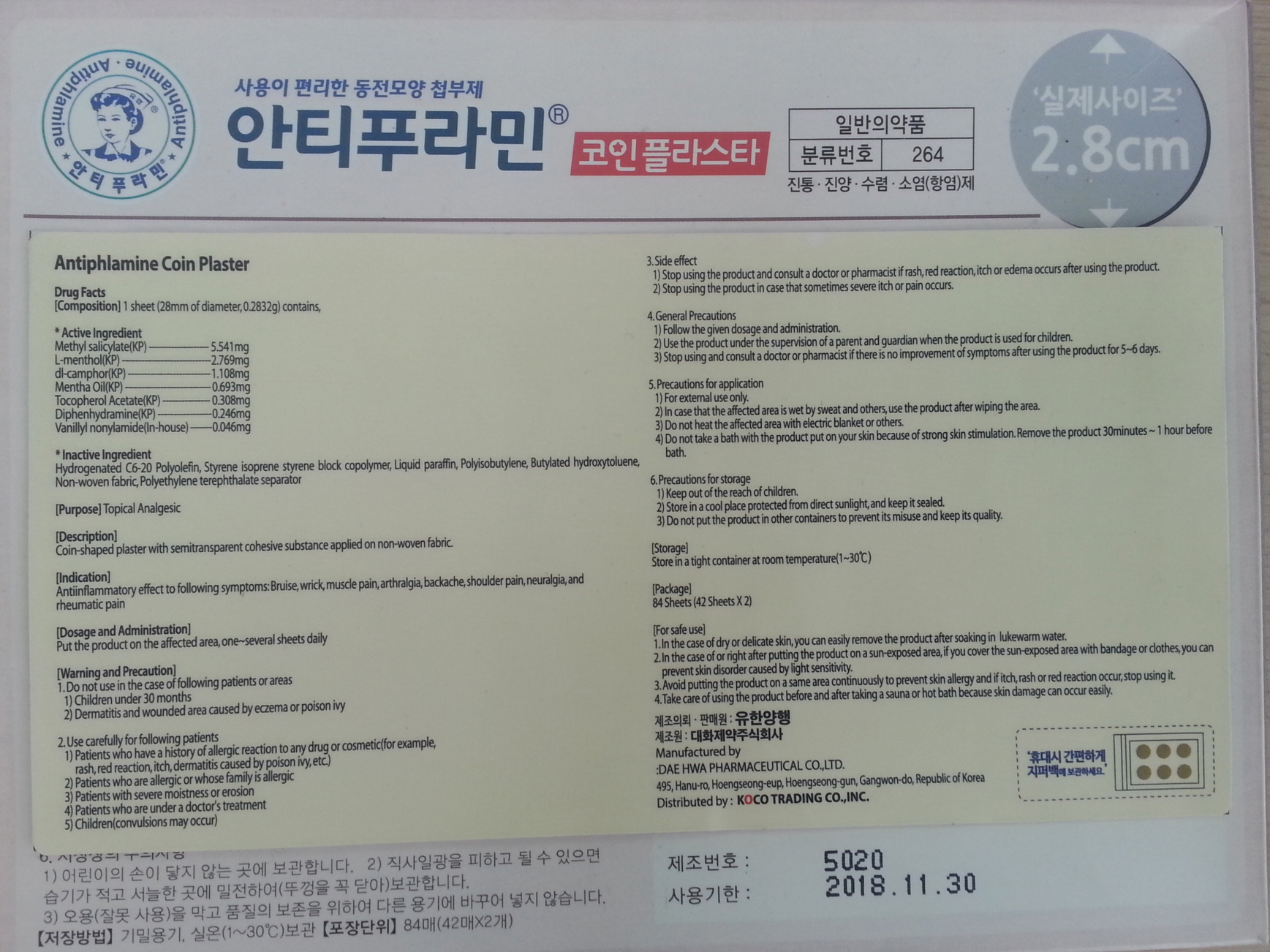 DRUG LABEL: Antiphlamine
NDC: 69642-1600 | Form: PATCH
Manufacturer: Hanul Trading Co., Ltd.
Category: otc | Type: HUMAN OTC DRUG LABEL
Date: 20170511

ACTIVE INGREDIENTS: LEVOMENTHOL 2.769 mg/0.2832 g; CAMPHOR (SYNTHETIC) 1.108 mg/0.2832 g; Diphenhydramine 0.246 mg/0.2832 g; .ALPHA.-TOCOPHEROL, DL- 0.308 mg/0.2832 g; Methyl Salicylate 5.541 mg/0.2832 g; Peppermint oil 0.693 mg/0.2832 g; Nonivamide 0.046 mg/0.2832 g
INACTIVE INGREDIENTS: MINERAL OIL

ACTIVE INGREDIENT

Active Ingredient: Methyl salicylate(KP) 5.541mg, L-menthol(KP), 2.769mg, dl-camphor(KP), 1.108mg, Mentha Oil(KP) 0.693mg, Tocopherol Acetate(KP) 0.308mg, Diphenhydramine(KP) 0.246mg, Vanillyl nonylamide(In-house) 0.046mg

INACTIVE INGREDIENT

[Inactive Ingredients] Hydrogenated C6-20 Polyolefin, Styrene isoprene styrene block copolymer, Liquid paraffin, Polyisobutylene, Butylated hydroxytoluene, Non-woven fabric, Polyethylene terephthalate separator

PURPOSE

[Purpose] Topical Analgesic

[Warnings and Precautions] 1. Do not use to following patients 1) Children under 30 months 2) Patients with wounds or damaged skin cause by eczema or poison ivy

2. Use carefully when using to following patients 1) Patients who have a history of allergic reaction to any drug or cosmetics 2) Patients who are allergic or whose family is allergic 3) Patients with severe moistness or erosion 4) Patients who are under a doctor's cure 5) Infant (Convulsions may occur)

3. Side effects 1) Stop using and ask doctor or pharmacist if rash, redness, itching, or edema occurs. 2) Stop using if sometimes severe itching or pain occurs.

4. General Precautions 1) Follow the given dosage and administration. 2) Use under adult's care for children. 3) Stop using and ask doctor or pharmacist if there is no improvement of symptoms in 5~6 days of using.

5. Precautions for application 1) For external use only. 2) Use after wiping if the affected part is wet. 3) Do not heat the affected part with electric blanket or any. 4) Do not take a bath with this drug attached. Remove it 30 min~1 hour before bath.

6. Precautions for storage 1) Keep out of the reach of children. 2) Store in a cool place out of direct sunlight, and keep it sealed. 3) Avoid misuse and do not put this product in a separate container for preservation of quality.

KEEP OUT OF REACH OF CHILDREN

Indications

[Indications] Anti-inflammatory effect to following symptoms: Bruise, wrick, muscle pain, arthralgia, backache, shoulder pain, neuralgia, and rheumatic pain.

DOSAGE & ADMINISTRATION

[Dosage and Administration] Put the product on the affected part, one~several sheets daily

OTHER SAFETY INFORMATION

[Description] Coin-shaped plaster with semitransparent cohesive substance applied on non-woven fabric.

[Storage] Store in tight container at room temperature(1~30℃)

[Package] 84 Sheets (42 Sheets X 2)

[Safe Administration] 1. If attached to dry or delicate skin, use lukewarm water when removing. 2. If attached to sun-exposed part, you can prevent extraordinary skin reaction by covering the part with a bandage or clothes. 3. Avoid using it to the same part continuously to prevent skin allergy. Stop using if itching, rash, or redness occurs. 4. Take care to avoid using before and after taking a sauna or hot massage.